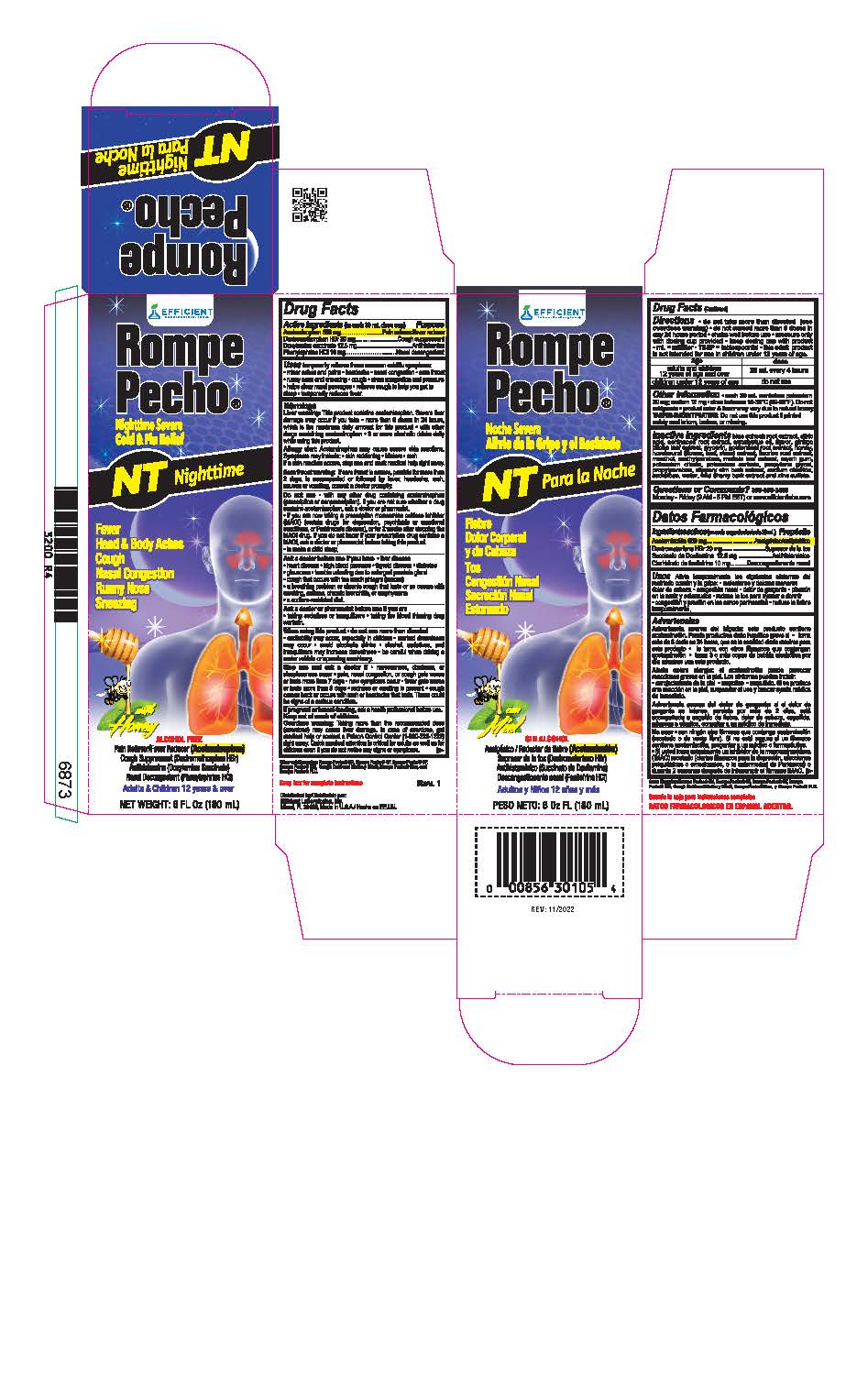 DRUG LABEL: Rompe Pecho
NDC: 58593-830 | Form: LIQUID
Manufacturer: EFFICIENT LABORATORIES INC
Category: otc | Type: HUMAN OTC DRUG LABEL
Date: 20250311

ACTIVE INGREDIENTS: ACETAMINOPHEN 650 mg/30 mL; DEXTROMETHORPHAN HYDROBROMIDE 20 mg/30 mL; DOXYLAMINE SUCCINATE 12.5 mg/30 mL; PHENYLEPHRINE HYDROCHLORIDE 10 mg/30 mL
INACTIVE INGREDIENTS: POTASSIUM CITRATE; MYRRH; POTASSIUM SORBATE; PROPYLENE GLYCOL; PROPYLPARABEN; ULMUS RUBRA BARK; MULLEIN LEAF; SODIUM CHLORIDE; SUCRALOSE; WATER; PRUNUS SEROTINA BARK; ZINC SULFATE; METHYLPARABEN; CAULOPHYLLUM THALICTROIDES ROOT; ECHINACEA, UNSPECIFIED; EUCALYPTUS OIL; GINKGO; GLYCERIN; GOLDENSEAL; HONEY; HOREHOUND; LICORICE; MENTHOL

Active ingredients (in each 30 mL dose cup)

Acetaminophen 650 mg

Dextromethorphan HBr 20 mg

Doxylamine Succinate 12.5 mg

Phenylephrine HCl 10 mg

Purpose

Paint reliever/fever reducer

Cough Suppressant

Antihistamine

Nasal decongestant

INDICATIONS AND USAGE

Uses temporarily relieves these common cold/flu symtoms:

- minor aches and pains
- headache
- nasal congestion
- sore throat
- runny nose and sneezing
- cough
- sinus congestion and pressure
- helps clear nasal passages
- relieves cough to help you get to sleep
- temporarily reduces fever

Warnings

Liver warning: This product contains acetaminophen. Sever liver damage may occur if you take

- more than 6 doses in 24 hours, which is the maximum daily amount for this product
- with other drugs containing acetaminophen
- 3 or more alcoholic drinks daily while using this product

Allergy alert: Acetaminophen may cause sever skin reactions. Symptoms may include:

- skin reddening
- blisters
- rash

If skin reaction occurs, stop use and seek medical help right away.

Sore throat warning: If sore throat is sever, persists for more than 2 days, is accompanied or followed by fever, headache, rash, nausea or vomiting, consult a doctor promptly

Do not use

- with any other drug containing acetaminophen (prescription or nonprescription). If you are not sure whether a drug contains acetaminphen, ask a doctor or pharmacist.
- if you are now taking a prescription monoamine oxidase inhibitor (MAOI) (certain drugs for depression, psychiatric or emotional conditions, or Parkinson's disease), or for 2 weeks after stopping the MAOI drug. If you do not know if you prescription drug contains a MAOI, ask a doctor or pharmalacist before taking this product.
- to make a child sleep

Ask a doctor before use if you have

- liver disease
- heart disease
- high blood pressure
- thyroid disease
- diabetes
- glaucoma
- trouble urinating due to enlarged prostate gland
- cough that occurs with too much phlegm (mucus)
- a breathing problem or chronic cough that lasts or as occurs with smoking, asthma, chronic bronchitis, or emphysema
- a sodium-restricted diet

Ask a doctor or pharmacist before use if you are

- taking sedatives or tranquilizers
- taking the blood thinning drug warfarin

When using this product

- do not use more than directed
- excitability may occur, especially in children
- marked draowsiness may occur
- acoid alcoholic drinks
- alcohol, sedatives, and tranquilizers may increase drowsiness
- be careful when driving a motor vehicle or operating machinery

Stop use and ask a doctor if

- nervousness, dizziness, or sleeplessness occur
- pain, nasal congestion, or cough gets worse or lasts more than 7 days
- new symptoms occur
- fever gets worse or lasts more than 3 days
- redness or swelling is present
- cough comes back or occurs with rash or headache that lasts. These could be signs of a serious condition.

Overdose warning: Taking more than the recommended dose (overdose) may cause liver damage. In case of overdose, get medical help or contact a Poison Control Center (1-800-222-1222) right away. Quick medical attention is critical for adults as well as for children even if you do not notice any signs or symptoms.

PREGNANCY OR BREAST FEEDING

If pregnant or breast-feeding, ask a health professional before use. Keep out of reach of children.

Keep out of reach of children.

Directions

- do not take more than directed (see Overdose warning)
- do not take more than 6 doses in any 24-hour period
- measure only with dosing cup provided. Do not use any other dosing device. Product color & flavor may vary due to natural honey.
- mL = milliliter
- shake well before use
- keep dosing cup with product
- Adults and Children 12 years & over: 30 mL every 4 hours
- Children under 12 years of age: do not use

INACTIVE INGREDIENT

Inactive ingredients: blue cohosh root extract, echinacea root extract, eucalyptus oil, flavor, ginkgo bilboa leaf extract, glycerin, goldenseal root extract, honey, horehouns (flower, leaf, stern) extract, licorice root extract, menthol, methylparaben, mullein leaf extract, myrrh gum, potassium citrate, potassium sorbate, propylene glycol, prolylparaben, slippery elm bark extract, sodium chloride, sucralose, water, wild cherry bark extract, zinc sulfate.

Questions or Comments? 305-805-3456

Monday - Friday (9 AM - 5 PM EST) or www.efficientlabs.com